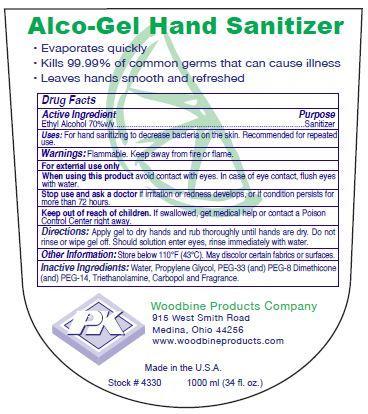 DRUG LABEL: Alco Hand Sanitizer
NDC: 11429-1003 | Form: GEL
Manufacturer: Woodbine Products Company
Category: otc | Type: HUMAN OTC DRUG LABEL
Date: 20250617

ACTIVE INGREDIENTS: ALCOHOL 70 mL/100 mL
INACTIVE INGREDIENTS: WATER; PROPYLENE GLYCOL; POLYETHYLENE GLYCOL 1500; POLYETHYLENE GLYCOL 400; POLYETHYLENE GLYCOL 700; TROLAMINE

Drug Facts 11429-1003

Active Ingredient

Ethyl Alcohol 70% v/v

Purpose

Sanitizer

Uses:

For hand sanitizing to decrease bacteria on the skin.

Recommended for repeated use.

Warnings:

Flammable. Keep away from fire or flame.

For external use only

When using this product avoid contact with eyes.

In case of eye contact, flush eyes with water.

Stop use and ask a doctor if irritation or redness develops, or if condition persists for more than 72 hours.

Keep out of reach of children.

If swallowed, get medical help or contact a Poison Control center right away.

Directions:

Apply gel to dry hands and rub thoroughly until hands are dry.

Do not rinse or wipe gel off.

Should solution enter eyes, rinse immediately with water.

Other Information:

Store below 110 F (43 C).

May discolor certain fabrics or surfaces.

Inactive Ingredients:

Water, Propylene Glycol, PEG-33 (and) PEG-8 Dimethicone (and) PEG-14, Triethanolamine, Carbopol and Fragrance.

PACKAGE LABEL

Alco-Gel Hand Sanitizer

Evaporates quickly

Kills 99.99% of common germs that can cause illness

Leaves hands smooth and refreshed

PK

Woodbine Products Company

915 West Smith Road

Medina, Ohio 44256

www.woodbineproducts.com

Made in the U.S.A.

Stock # 4330 10000 ml (34 fl. oz.)